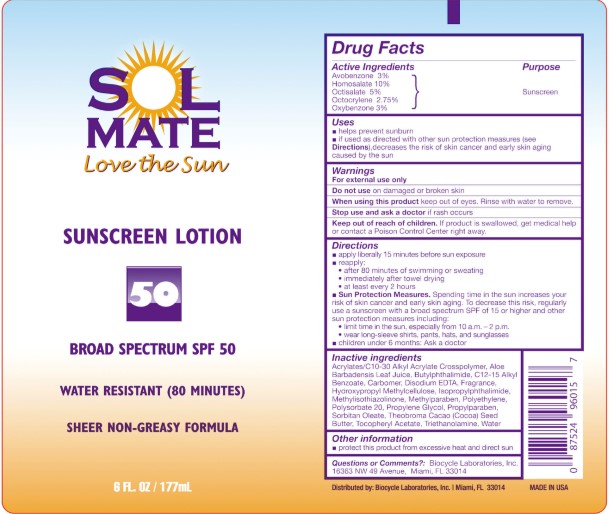 DRUG LABEL: SolMate
NDC: 58443-0116 | Form: LOTION
Manufacturer: Prime Enterprises Inc.
Category: otc | Type: HUMAN OTC DRUG LABEL
Date: 20201014

ACTIVE INGREDIENTS: AVOBENZONE 29.7 mg/1 mL; OCTISALATE 49.5 mg/1 mL; OCTOCRYLENE 27.225 mg/1 mL; HOMOSALATE 99 mg/1 mL; OXYBENZONE 29.7 mg/1 mL
INACTIVE INGREDIENTS: FRAGRANCE LAVENDER & CHIA F-153480; HYPROMELLOSE, UNSPECIFIED; SORBITAN MONOOLEATE; POLYSORBATE 20; COCOA BUTTER; WATER; PROPYLENE GLYCOL; ALOE VERA LEAF; .ALPHA.-TOCOPHEROL ACETATE; HIGH DENSITY POLYETHYLENE; CARBOMER INTERPOLYMER TYPE A (ALLYL SUCROSE CROSSLINKED); ALKYL (C12-15) BENZOATE; CARBOMER 980; METHYLISOTHIAZOLINONE; ISOPROPYLPHTHALIMIDE; N-BUTYLPHTHALIMIDE; EDETATE DISODIUM ANHYDROUS; METHYLPARABEN; PROPYLPARABEN; TROLAMINE

SolMate Sunscreen Lotion Broad Spectrum SPF 50

Active Ingredients

Avobenzone 3%

Homosalate 10%

Octisalate 5%

Octocrylene 2.75%

Oxybenzone 3%

Purpose

Sunscreen

Uses

• helps prevent sunburn

• if used as directed with other sun protection measures (See Directions), decreases the risk of skin cancer and early skin aging caused by the sun.

Warnings

For external use only

Do not use on damaged or broken skin

When using this product keep out of eyes. Rinse with water to remove.

Stop use and ask a doctor if rash occurs

Keep out of reach of children. If product is swallowed, get medical help or contact a Poison Control Center right away.

Directions

• apply liberally 15 minutes before sun exposure

• reapply:

• after 80 minutes of swimming or sweating

• immediately after towel drying

• at least every 2 hours

• Sun Protection Measures. Spending time in the sun increases your risk of skin cancer and early skin aging. To decrease this risk, regularly use a sunscreen with broad spectrum SPF of 15 or higher and other sun protection measures including:

• limit time in the sun, especially from 10 a.m. – 2 p.m.

• wear long-sleeve shirts, pants, hats, and sunglasses

• children under 6 months: Ask a doctor

Inactive ingredients

Acrylates/C10-30 Alkyl Acrylate Crosspolymer, Aloe Barbadensis Leaf Juice, Butylphthalimide, C12-15 Alkyl Benzoate, Carbomer, Disodium EDTA, Fragrance, Hydroxypropyl Methylcellulose, Isopropylphthalimide, Methylisothiazolinone, Methylparaben, Polyethylene, Polysorbate 20, Propylene Glycol, Propylparaben, Sorbitan Oleate, Theobroma Cacao (Cocoa) Seed Butter, Tocopheryl Acetate, Triethanolamine, Water

Other information

• protect this product from excessive heat and direct sun

Questions and comments?

Biocycle Laboratories, Inc.

16363 NW 49 Avenue, Miami, Fl 33014